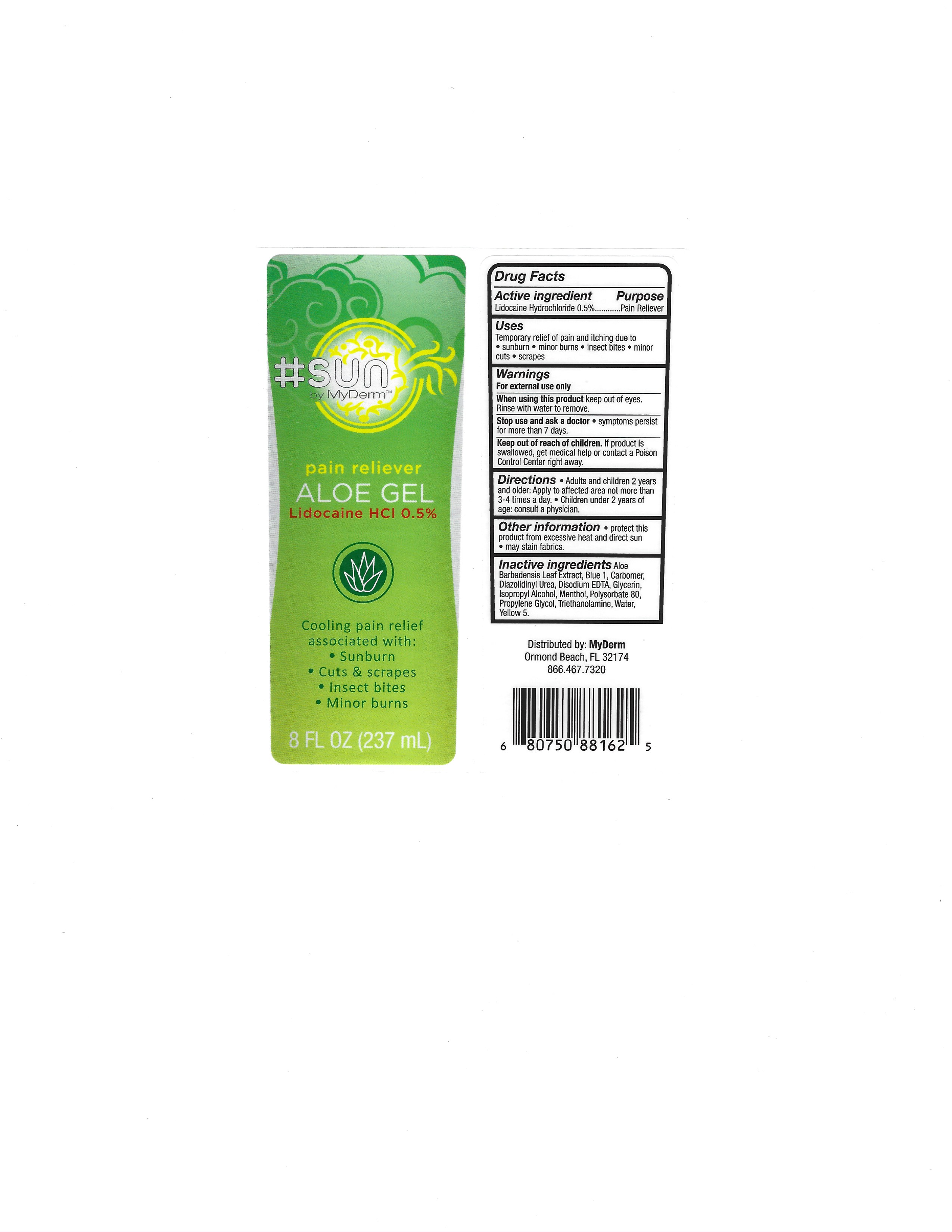 DRUG LABEL: MyDerm
NDC: 72667-008 | Form: GEL
Manufacturer: Inspec Solutions LLC.
Category: otc | Type: HUMAN OTC DRUG LABEL
Date: 20250618

ACTIVE INGREDIENTS: LIDOCAINE HYDROCHLORIDE 0.5 g/100 mL
INACTIVE INGREDIENTS: WATER; GLYCERIN; ISOPROPYL ALCOHOL; MENTHOL; PROPYLENE GLYCOL 2-STEARATE; TROLAMINE SALICYLATE; ALOE VERA LEAF; CARBOMER 1342; DIAZOLIDINYL UREA; DISODIUM HEDTA; POLYSORBATE 80; FD&C YELLOW NO. 5 FREE ACID

MyDerm Pain Reliever Aloe Gel Lidocaine HCI 0.5%

Active Ingredient

Lidocaine ............. 0.5%

PURPOSE

Lidocaine 0.5% ............. Pain Reliever

INDICATIONS AND USAGE

Temporary relief of pain and itching due to

- sunburn - minor burn - insect bites - minor cuts - scraps

Warnings

For external use only

When using this product keep out of eyes

Rinse with warter to remove

Sop use and ask a doctor

system persist for more than 7 days.

Keep out of reach of children. If product is swallowed, get medical help or contact a poison control center right away.

DOSAGE AND ADMINISTRATION

Direction

Adults and children 2 years and older: aooly to affected area not more that 3-4 times a day

Children under 2 years of age: consult a physician.

INACTIVE INGREDIENT

Inactive Ingredients: Aloe Barbadensis Leaf Extract, Carbomer, Diazolidinyl Urea, Disodium EDTA, Glycerin, Isopropyl Alcohol, Menthol, Polysorbate 80, Propylene Glycol, Triethanolamine, Water, Yellow 5.